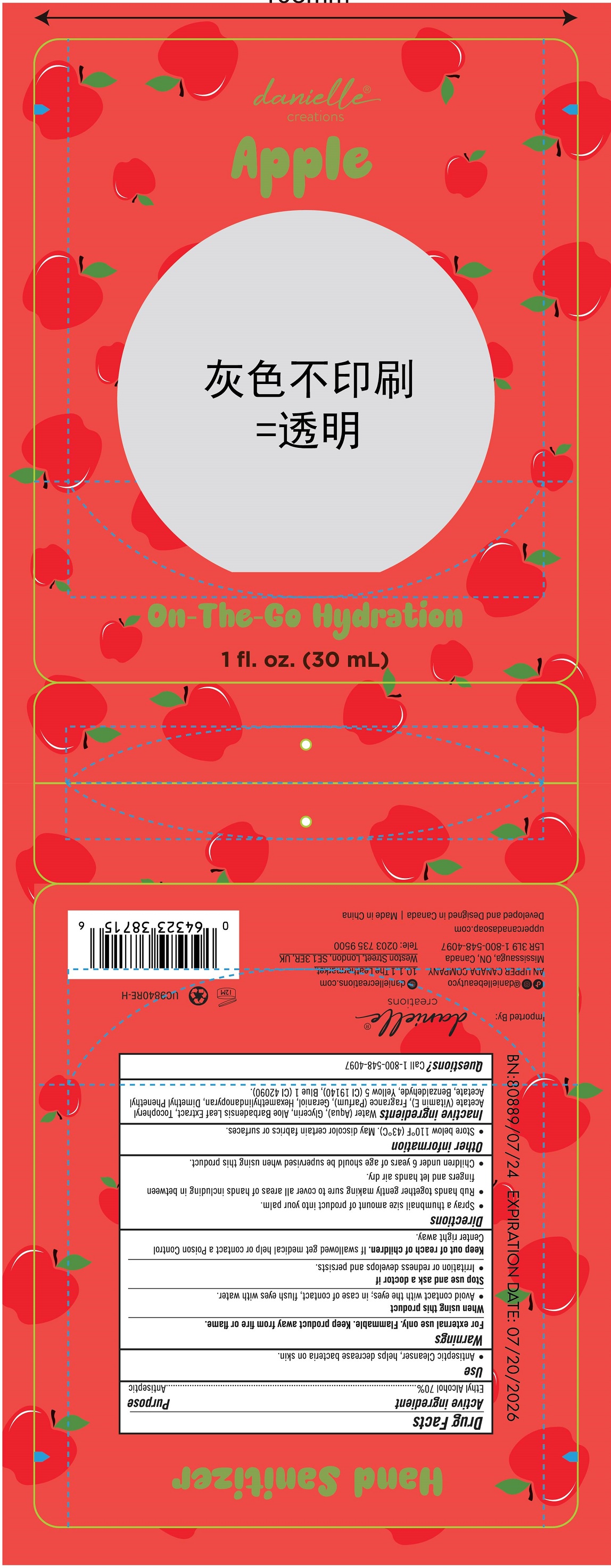 DRUG LABEL: Danielle Creations Hand Sanitizer - Apple
NDC: 56136-448 | Form: SPRAY
Manufacturer: Ganzhou Olivee Cosmetic Co., Ltd.
Category: otc | Type: HUMAN OTC DRUG LABEL
Date: 20240910

ACTIVE INGREDIENTS: ALCOHOL 70 mL/100 mL
INACTIVE INGREDIENTS: WATER; GLYCERIN; .ALPHA.-TOCOPHEROL ACETATE, D-; GERANIOL; HEXAMETHYLINDANOPYRAN; BENZALDEHYDE; FD&C YELLOW NO. 5; FD&C BLUE NO. 1

30ml apple hand sanitizer

Active ingredient

Ethyl Alcohol 70%

Purpose

Antiseptic

Use

Antiseptic cleanser, helps decrease bacteria on hands.

Warnings

For external use only.

Flammable.Keep product away from fire or flame.

When using this product

avoid contact with eyes; in case of contact, flush eyes with water.

Stop use and ask a doctor if

irritation or redness develops and persists.

Keep out of reach of children.

If swallowed, get medical help or contact a Poison Control Center right away.

Directions

- Spray a tubnail size amount of product into your palm.
- Rub hands together gently making sure to cover all areas of hands including in between fingers and let hands air dry.
- children under 6 years of age should be supervised when using this product.

Inactive ingredients

Water (Aqua), Glycerin, Aloe Barbadensis Leaf Extract, Tocopheryl Acetate (Vitamin E), Fragrance (Parfum), Geraniol, Hexamethylindanopyran, Dimethyl Pherethyl Acetate, Benzaldehyde, Yellow 5 (Cl 19140), Blue 1 (CI 42090).

Store below 110℉（43℃）. May discolor certain fabrics or surfaces.

Questions? 1-800-548-4097